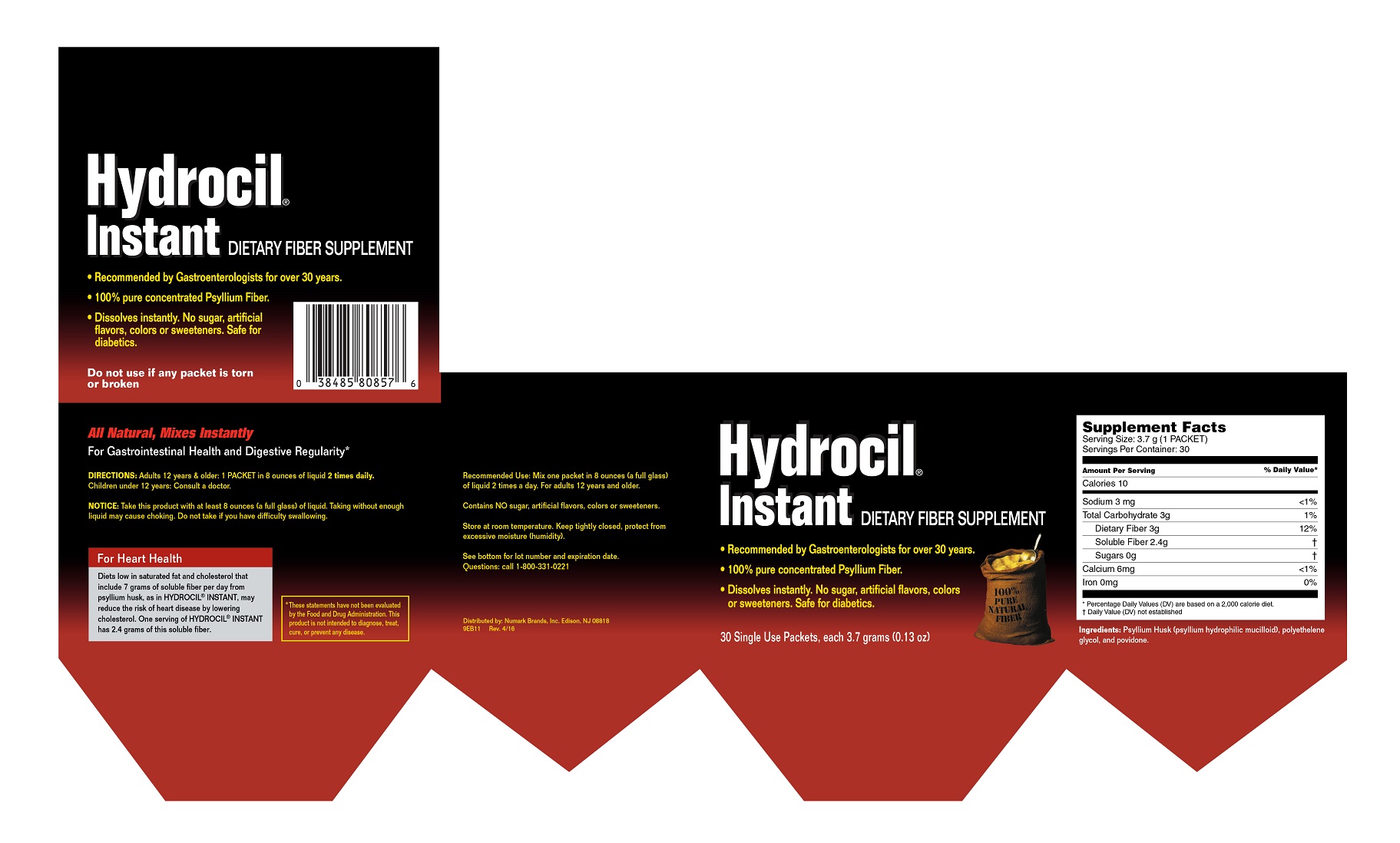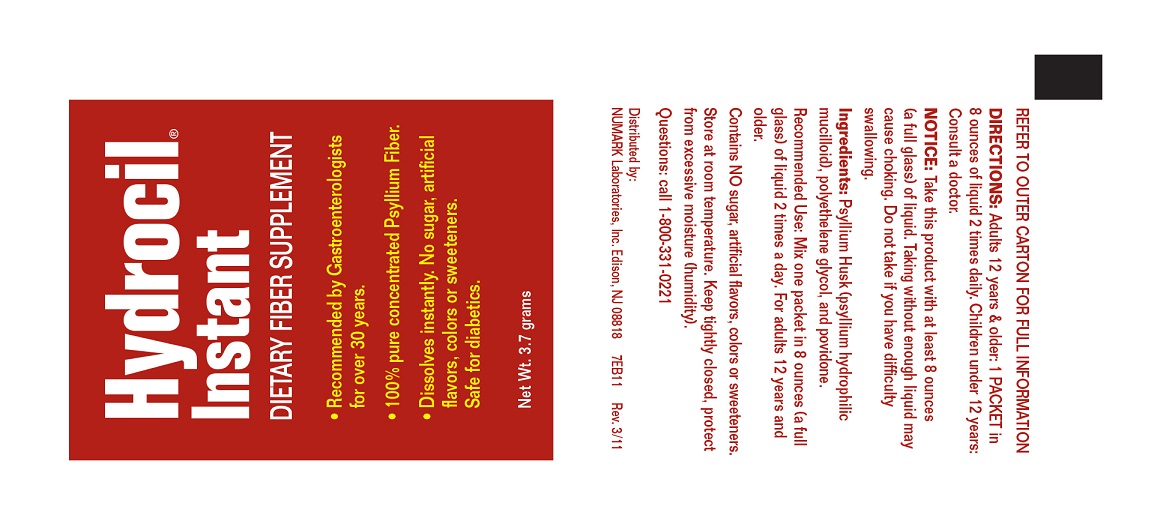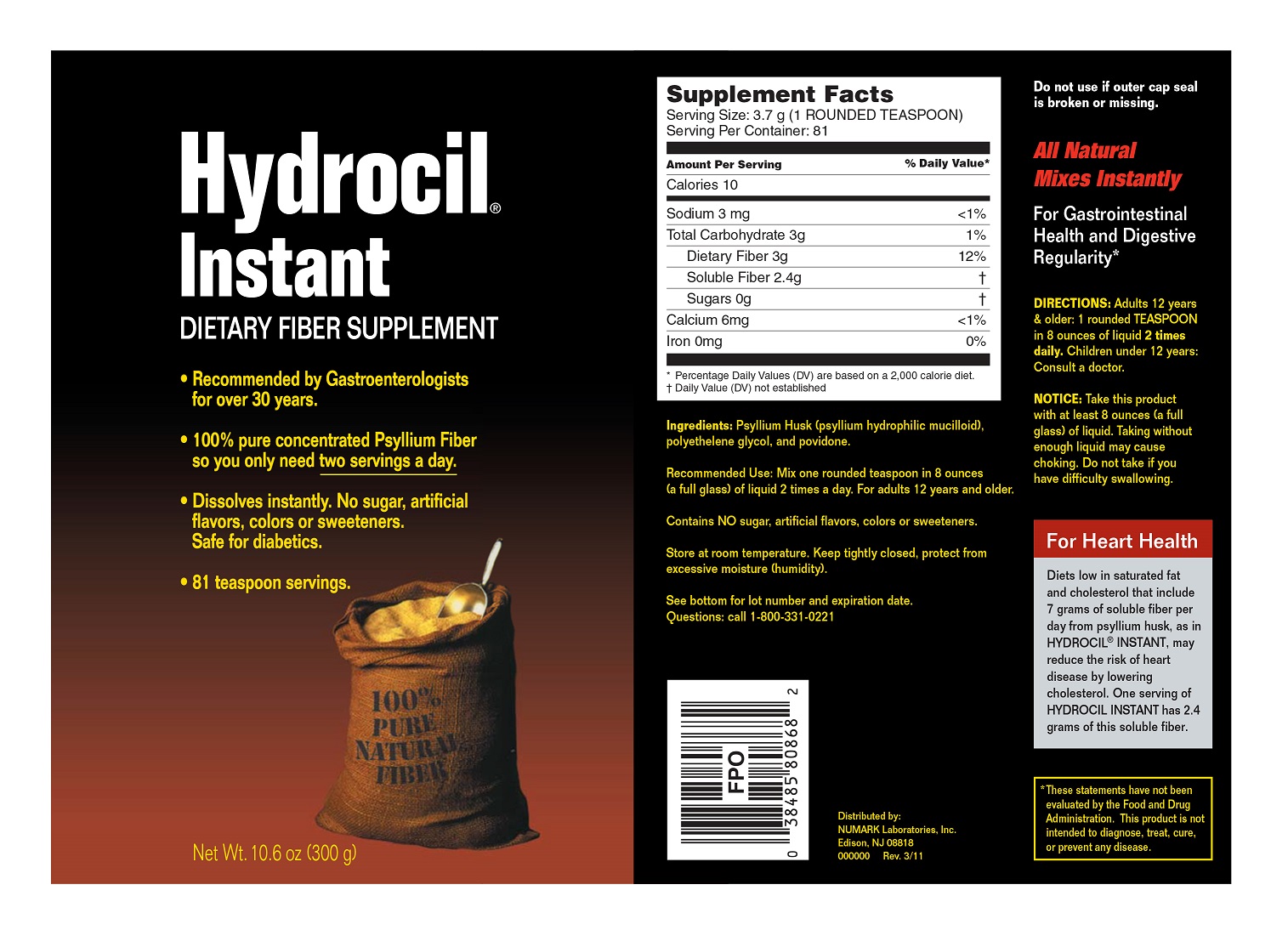 DRUG LABEL: Hydrocil Instant Dietary Fiber Supplement 
NDC: 69846-808 | Form: POWDER
Manufacturer: NUMARK BRANDS, INC
Category: other | Type: DIETARY SUPPLEMENT
Date: 20160802

ACTIVE INGREDIENTS: Plantago Seed 1 g/1 g
INACTIVE INGREDIENTS: Polyethylene Glycols; Povidones

Hydrocil Instant Dietary Fiber Supplement

Supplement Facts - Single Use Packets

Dietary Fiber Supplement

Serving Size: 3.7 g (1 PACKET)

Servings Per Container: 30

Amount per Serving | % Daily Value [Percentage Daily Values are based on a 2000 calorie diet.]
Calories 10
Sodium 3 mg | < 1%
Total Carbohydrate 3g | 1%
Dietary Fiber 3g | 12%
Soluble Fiber 2.4g | [Daily Value (DV) not established]
Sugars 0g
Calcium 6mg | <1%
Iron 0mg | 0%

Ingredients: Psyllium Husk (psyllium hydrophilic mucilloid), polyethelene glycol, and povidone.

DIRECTIONS - Singe Use Packets:

Adults 12 years & older: 1 PACKET in 8 ounces of liquid 2 times daily.

Children under 12 years: Consult a doctor.

Supplement Facts - Powder

Dietary Fiber Supplement

Serving Size: 3.7 g (1 ROUNDED TEASPOON)

Servings Per Container: 81

Amount per Serving | % Daily Value [Percentage Daily Values are based on a 2000 calorie diet.]
Calories 10
Sodium 3 mg | < 1%
Total Carbohydrate 3g | 1%
Dietary Fiber 3g | 12%
Soluble Fiber 2.4g | [Daily Value (DV) not established]
Sugars 0g
Calcium 6mg | <1%
Iron 0mg | 0%

Ingredients: Psyllium Husk (psyllium hydrophilic mucilloid), polyethelene glycol, and povidone.

DIRECTIONS - Powder:

Adults 12 years & older: 1 rounded TEASPOONT in 8 ounces of liquid 2 times daily.

Children under 12 years: Consult a doctor.

NOTICE:

Take this product with at least 8 ounces (a full glass) of liquid. Taking without enough liquid may cause choking. Do not take if you have difficulty swallowing.

SAFE HANDLING WARNING

Store at room temperature. Keep tightly closed, protect from excessive moisture (humidity).

See bottom for lot number and expiration date.

Questions: call 1-800-331-0221

HEALTH CLAIM

All Natural, Mixes Instantly

For Gastrointestinal Health and Digestive Regularity*

For Heart Health

Diets low in saturated fat and cholesterol that include 7 grams of soluble fiber per day from psyllium husk, as in HYDROCIL® INSTANT, may reduce the risk of heart disease by lowering cholesterol. One serving of HYDROCIL® INSTANT has 2.4 grams of this soluble fiber.

* These statements have not been evaluated by the Food and Drug Administration. This product is not intended to diagnose, treat, cure, or prevent any disease.

PRINCIPAL DISPLAY PANEL

Hydrocil®
Instant DIETARY FIBER SUPPLEMENT
• Recommended by Gastroenterologists for over 30 years.
• 100% pure concentrated Psyllium Fiber.
• Dissolvers instantly. No sugar, artificial flavors, colors or sweeteners. Safe for diabetics.
30 Single Use Packets, each 3.7 grams (0.13 oz)
Do not use if any packet is torn or broken
Recommended Use: Mix one packet in 8 ounces (a full glass) of liquid 2 times a day. For adults 12 years and older.
Contains NO sugar, artificial flavors, colors or sweeteners.
Distributed by: Numark Brands, Inc. Edison, NJ 08818
9EB11 Rev. 4/16

Hydrocil®
Instant
DIETARY FIBER SUPPLEMENT
• Recommended by Gastroenterologists for over 30 years.
• 100% pure concentrated Psyllium Fiber.
• Dissolvers instantly. No sugar, artificial flavors, colors or sweeteners. Safe for diabetics.
Net Wt. 3.7 grams
REFER TO OUTER CARTON FOR FULL INFORMATION
Contains NO sugar, artificial flavors, colors or sweeteners.
Distributed by:
Numark Brands, Inc. Edison, NJ 08818
7EB11 Rev. 3/11

Hydrocil®
Instant DIETARY FIBER SUPPLEMENT
• Recommended by Gastroenterologists for over 30 years.
• 100% pure concentrated Psyllium Fiber so you only need two servings day.
• Dissolvers instantly. No sugar, artificial flavors, colors or sweeteners. Safe for diabetics.
81 teaspoon servings.
Net Wt. 10.6 oz (300 g)
Do not use if outer cap seal is broken or missing.
Recommended Use: Mix one teaspoon in 8 ounces (a full glass) of liquid 2 times a day. For adults 12 years and older.
Contains NO sugar, artificial flavors, colors or sweeteners.
Distributed by:
Numark Brands, Inc.
Edison, NJ 08818
000000 Rev. 3/11